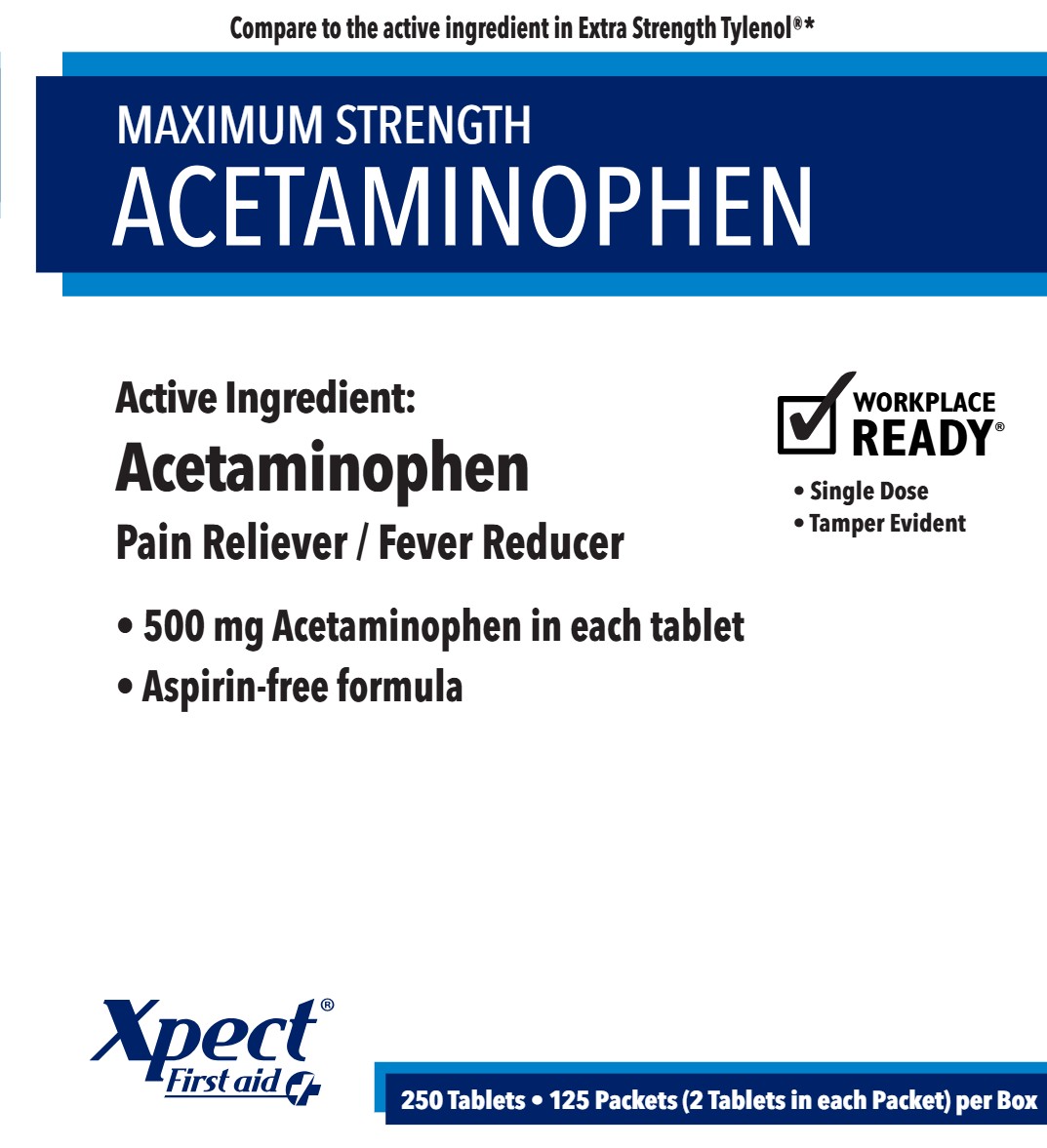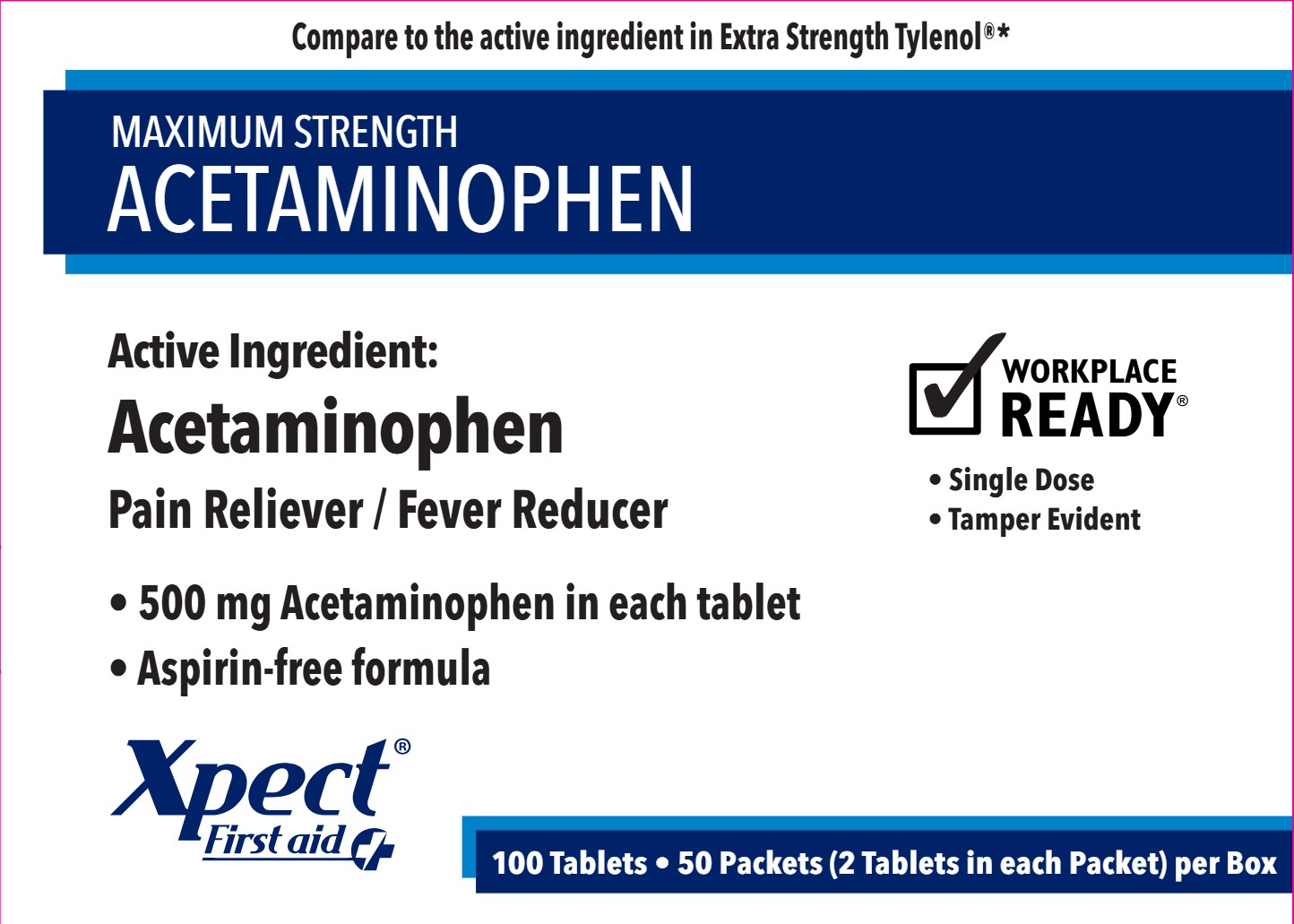 DRUG LABEL: Xpect Acetaminophen
NDC: 42961-399 | Form: TABLET
Manufacturer: Cintas Corporation
Category: otc | Type: HUMAN OTC DRUG LABEL
Date: 20250922

ACTIVE INGREDIENTS: ACETAMINOPHEN 500 mg/1 1
INACTIVE INGREDIENTS: CASTOR OIL; STARCH, CORN; HYPROMELLOSE, UNSPECIFIED; POLYETHYLENE GLYCOL, UNSPECIFIED; POVIDONE, UNSPECIFIED; SODIUM STARCH GLYCOLATE TYPE A; STEARIC ACID; TITANIUM DIOXIDE

Xpect Acetaminophen

Active ingredient (in each tablet)

Acetaminophen 500 mg

Purpose

Pain reliever/fever reducer

Uses

- temporarily relieves minor aches and pains due to: headache, the common cold, backache, minor pain of arthritis, toothache, muscular aches, premenstrual and menstrual cramps
- temporarily reduces fever

Warnings

Liver warning: This product contains acetaminophen. Severe liver damage may occur if you take

- more than 4,000 mg of acetaminophen in 24 hours
- with other drugs containing acetaminophen
- 3 or more alcoholic drinks every day while using this product

Allergy alert: Acetaminophen may cause severe skin reactions. Symptoms may include:

- skin reddening
- blisters
- rash

If a skin reaction occurs, stop use and seek medical help right away.

Do not use

- with any other drug containing acetaminophen (prescription or nonprescription). If you are not sure whether a drug contains acetaminophen, ask a doctor or pharmacist.
- if you are allergic to acetaminophen or any of the inactive ingredients in this product

Ask a doctor before use if you have

liver disease.

Ask a doctor or pharmacist before use if you are

taking the blood thinning drug warfarin.

Stop use and ask a doctor if

- pain gets worse or lasts more than 10 days
- fever gets worse or lasts more than 3 days
- new symptoms occur
- redness or swelling is present

These could be signs of a serious condition.

If pregnant or breast-feeding,

ask a health professional before use.

Keep out of reach of children.

In case of accidental overdose, get medical help or contact a Poison Control Center right away. Prompt medical attention is critical for adults as well as for children even if you do not notice any signs or symptoms.

Directions

- do not take more than directed
- adults and children 12 years and over: take 2 tablets every 6 hours while symptoms last; do not take more than 6 tablets in 24 hours, unless directed by a doctor; do not take for more than 10 days unless directed by a doctor
- children under 12 years: ask a doctor

Other information

- store at 25°C (77°F); excursions permitted between 15°-30°C (59°-86°F)
- see packet for expiration date and lot number

Inactive ingredients

castor oil, corn starch, hypromellose, polyethylene glycol, povidone, pregelatinized starch, sodium starch glycolate, starch, steric acid, titanium dioxide

Questions?

1-877-973-2811 Monday-Friday 8:00 AM-5:00 PM

50 Packets

Compare to the active ingredient in Extra Strength Tylenol®*

MAXIMUM STRENGTH

ACETAMINOPHEN

Active Ingredient:

Acetaminophen

Pain Reliever / Fever Reducer

- 500 mg Acetaminophen in each tablet
- Aspirin-free formula

Xpect® First aid

WORKPLACE READY®

- Single Dose
- Tamper Evident

100 Tablets • 50 Packets (2 Tablets in each Packet) per Box

125 Packets

Compare to the active ingredient in Extra Strength Tylenol®*

MAXIMUM STRENGTH

ACETAMINOPHEN

Active Ingredient:

Acetaminophen

Pain Reliever / Fever Reducer

- 500 mg Acetaminophen in each tablet
- Aspirin-free formula

Xpect® First aid

WORKPLACE READY®

- Single Dose
- Tamper Evident

250 Tablets • 125 Packets)2 Tablets in each Packet) per Box